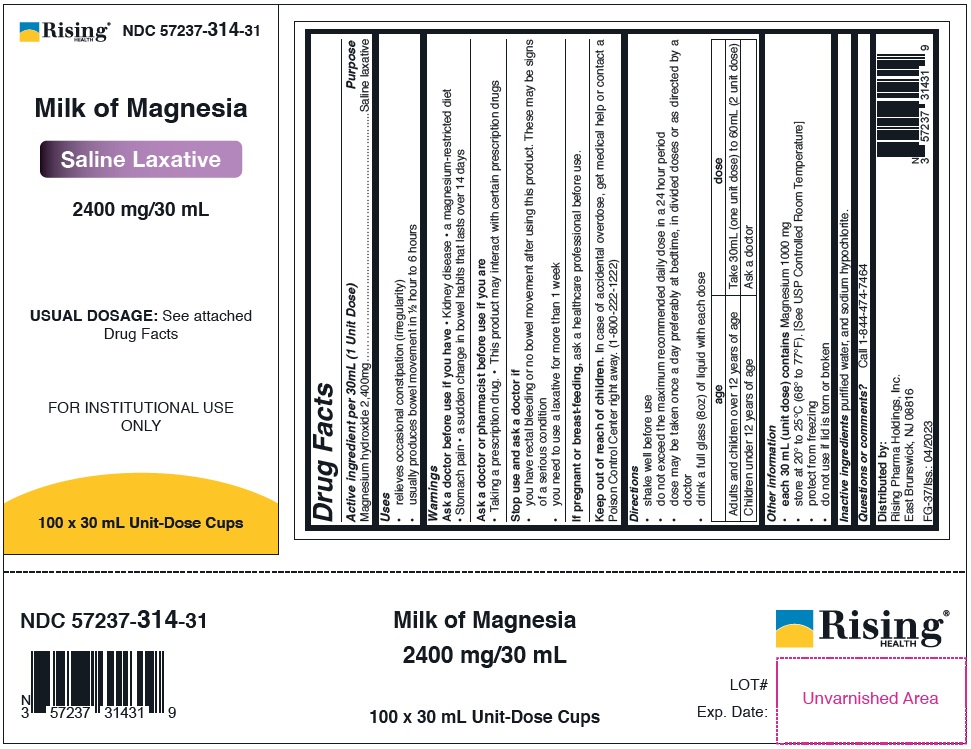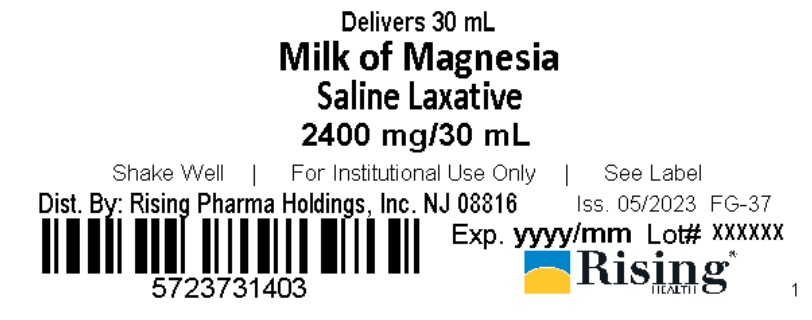 DRUG LABEL: Milk of Magnesia
NDC: 57237-314 | Form: SUSPENSION
Manufacturer: Rising Pharma Holdings, Inc.
Category: otc | Type: HUMAN OTC DRUG LABEL
Date: 20250701

ACTIVE INGREDIENTS: MAGNESIUM HYDROXIDE 2400 mg/30 mL
INACTIVE INGREDIENTS: WATER; SODIUM HYPOCHLORITE

Milk of Magnesia 2400 mg/30 mL

Drug Facts

Active ingredient per 30mL (1 Unit Dose)

Magnesium hydroxide 2,400 mg

Purpose

Saline laxative

Uses

• relieves occasional constipation (irregularity)

• usually produces bowel movement in ½ hour to 6 hours

Warnings

Ask a doctor before use if you have • Kidney disease • a magnesium-restricted diet • Stomach pain • a sudden change in bowel habits that lasts over 14 days

Ask a doctor or pharmacist before use if you are

• Taking a prescription drug. • This product may interact with certain prescription drugs

Stop use and ask a doctor if

• you have rectal bleeding or no bowel movement after using this product. These may be signs of a serious condition

• you need to use a laxative for more than 1 week

PREGNANCY OR BREAST FEEDING

If pregnant or breast-feeding, ask a health professional before use.

Keep out of reach of children. In case of accidental overdose, get medical help or contact a Poison Control Center right away. (1-800-222-1222)

Directions

• shake well before use

• do not exceed the maximum recommended daily dose in a 24 hour period

• dose may be taken once a day preferably at bedtime, in divided doses or as directed by a doctor

• drink a full glass (8oz) of liquid with each dose

age | dose
Adults and children over 12 years of age | Take 30mL (one unit dose) to 60mL (2 unit dose)
Children under 12 years of age | Ask a doctor

Other information

• each 30 mL (unit dose) contains Magnesium 1000 mg

• store at 20° to 25°C (68° to 77°F). [See USP Controlled Room Temperature]

• protect from freezing

• do not use if lid is torn or broken

Inactive ingredients purified water, and sodium hypochlorite.

NDC Information -

2400 mg/30 mL

Each 30 mL of Milk of Magnesia contains Magnesium hydroxide 2,400mg and is supplied in the following oral dosage forms:

NDC 57237-314-03 unit dose cup 30mL
NDC 57237-314-31 (100x30) unit dose cups 30mL

Questions or comments?Call 1-844-474-7464

Distributed by:
Rising Pharma Holdings, Inc.
East Brunswick, NJ 08816

FG-37/Iss.: 04/2023

PACKAGE LABEL.PRINCIPAL DISPLAY PANEL

2400 mg/30 mL

Lid Label NDC 57237-314-03

2400 mg/30 mL

Case Label NDC 57237-314-31